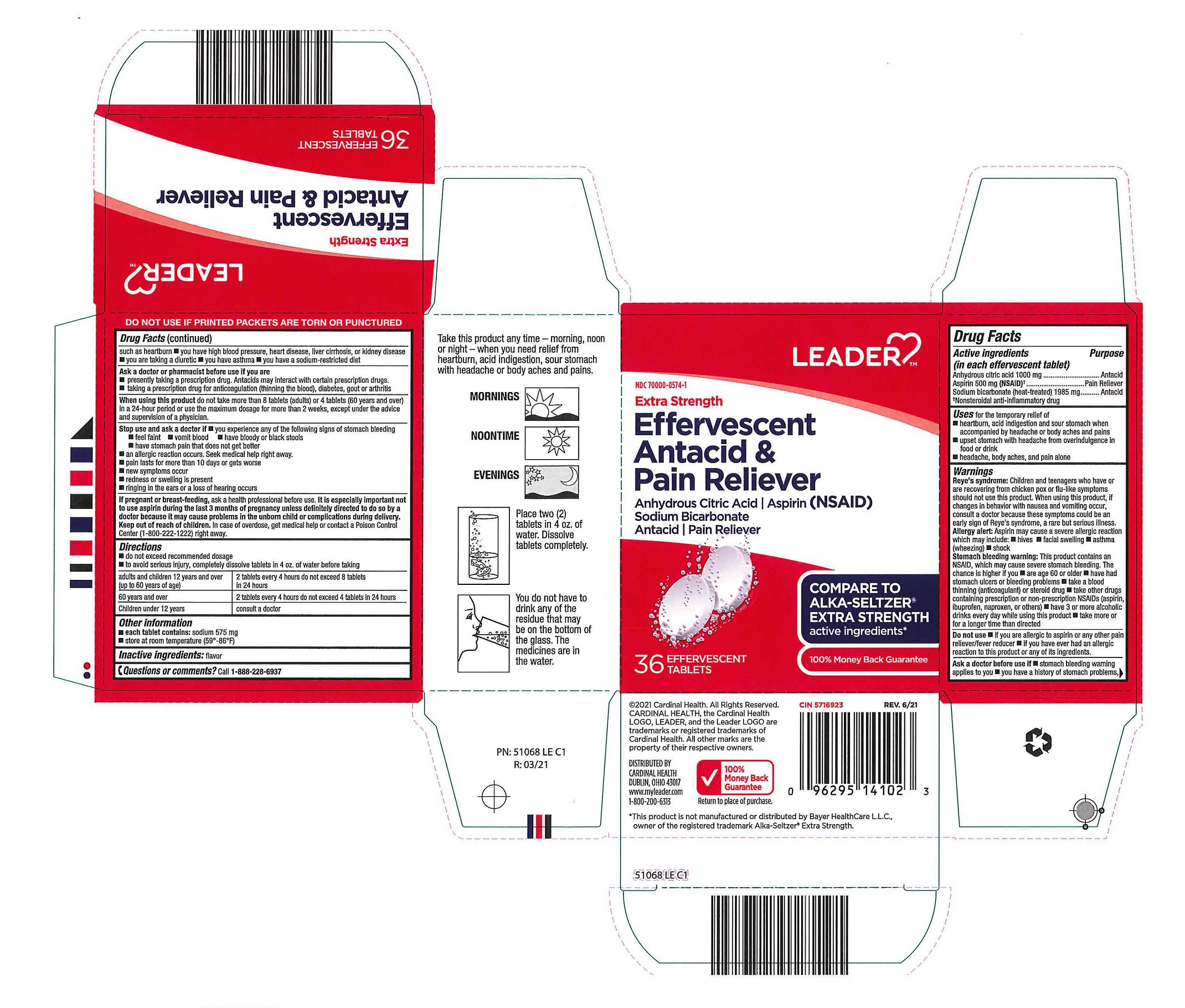 DRUG LABEL: Leader Extra Strength Effervescent Antacid and Pain Reliever
NDC: 70000-0574 | Form: TABLET, EFFERVESCENT
Manufacturer: Cardinal Health
Category: otc | Type: HUMAN OTC DRUG LABEL
Date: 20260225

ACTIVE INGREDIENTS: SODIUM BICARBONATE 1985 mg/1 1; ASPIRIN 500 mg/1 1; ANHYDROUS CITRIC ACID 1000 mg/1 1
INACTIVE INGREDIENTS: LEMON

Leader Extra Strength Effervescent Antacid & Pain Reliever

Active ingredients

(in each effervescent tablet)

Anhydrous citric acid 1000 mg

Aspirin 500 mg (NSAID)*

Sodium bicarbonate (heat-treated) 1985 mg

*Nonsteroidal anti-inflammatory drug

Purpose

(in each effervescent tablet)

Anhydrous citric acid 1000 mg..............................................................Antacid

Aspirin 500 mg (NSAID)*......................................................................Pain Reliever

Sodium bicarbonate (heat-treated) 1985 mg........................................Antacid

*Nonsteroidal anti-inflammatory drug

Uses

Uses for the temporary relief of

■ heartburn, acid indigestion and sour stomach when accompanied by headache or body aches and pains

■ upset stomach with headache from overindulgence in food or drink

■ headache, body aches and pain alone

Warnings

Reye’s syndrome: Children and teenagers who have or are recovering from chicken pox or flu-like symptoms should not use this product. When using this product, if changes in behavior with nausea and vomiting occur, consult a doctor because these symptoms could be an early sign of Reye’s syndrome, a rare but serious illness.

Allergy alert: Aspirin may cause a severe allergic reaction which may include: ■ hives ■ facial swelling ■ asthma (wheezing) ■ shock

Stomach bleeding warning: This product contains an NSAID, which may cause severe stomach bleeding. The chance is higher if you ■ are age 60 or older ■ have had stomach ulcers or bleeding problems ■ take a blood thinning (anticoagulant) or steroid drug

■ take other drugs containing prescription or nonprescription NSAIDs (aspirin, ibuprofen, naproxen, or others) ■ have 3 or more alcoholic drinks every day while using this product ■ take more or for a longer time than directed

Do not use

■ if you are allergic to aspirin or any other pain reliever/fever reducer

■ if you have ever had an allergic reaction to this product or any of its ingredients.

Ask a doctor before use if

■ stomach bleeding warning applies to you ■ you have a history of stomach problems, such as heartburn ■ you have high blood pressure, heart disease, liver cirrhosis, or kidney disease ■ you are taking a diuretic ■ you have asthma ■ you have a sodium-restricted diet

Ask a doctor or pharmacist before use if you are

■ presently taking a prescription drug. Antacids may interact with certain prescription drugs.

■ taking a prescription drug for anticoagulation (thinning the blood), diabetes, gout or arthritis

When using this product do not take more than 8 tablets (adults) or 4 tablets (60 years and over) in a 24-hour period or use the maximum dosage for more than 2 weeks, except under the advice and supervision of a physician.

Stop use and ask a doctor if ■ you experience any of the following signs of stomach bleeding

■ feel faint ■ vomit blood ■ have bloody or black stools

■ have stomach pain that does not get better

■ an allergic reaction occurs. Seek medical help right away.

■ pain lasts for more than 10 days or gets worse

■ new symptoms occur

■ redness or swelling is present

■ ringing in the ears or a loss of hearing occurs

If pregnant or breast-feeding, ask a health professional before use. It is especially important not to use aspirin during the last 3 months of pregnancy unless definitely directed to do so by a doctor because it may cause problems in the unborn child or complications during delivery.

OVERDOSAGE

In case of overdose, get medical help or contact a Poison Control Center (1-800-222-1222) right away.

Directions

■ do not exceed recommended dosage

■ to avoid serious injury, completely dissolve tablets in 4 oz. of water before taking

adults and children 12 years and over (up to 60 years of age): 2 tablets every 4 hours - do not exceed 8 tablets in 24 hours

60 years and over: 2 tablets every 4 hours - do not exceed 4 tablets in 24 hours

Children under 12 years: consult a doctor

Other information

■ each tablet contains: sodium 575 mg

■ store at room temperature (59º-86ºF)

Inactive ingredients

flavor

Questions or comments?

1-888-228-6937